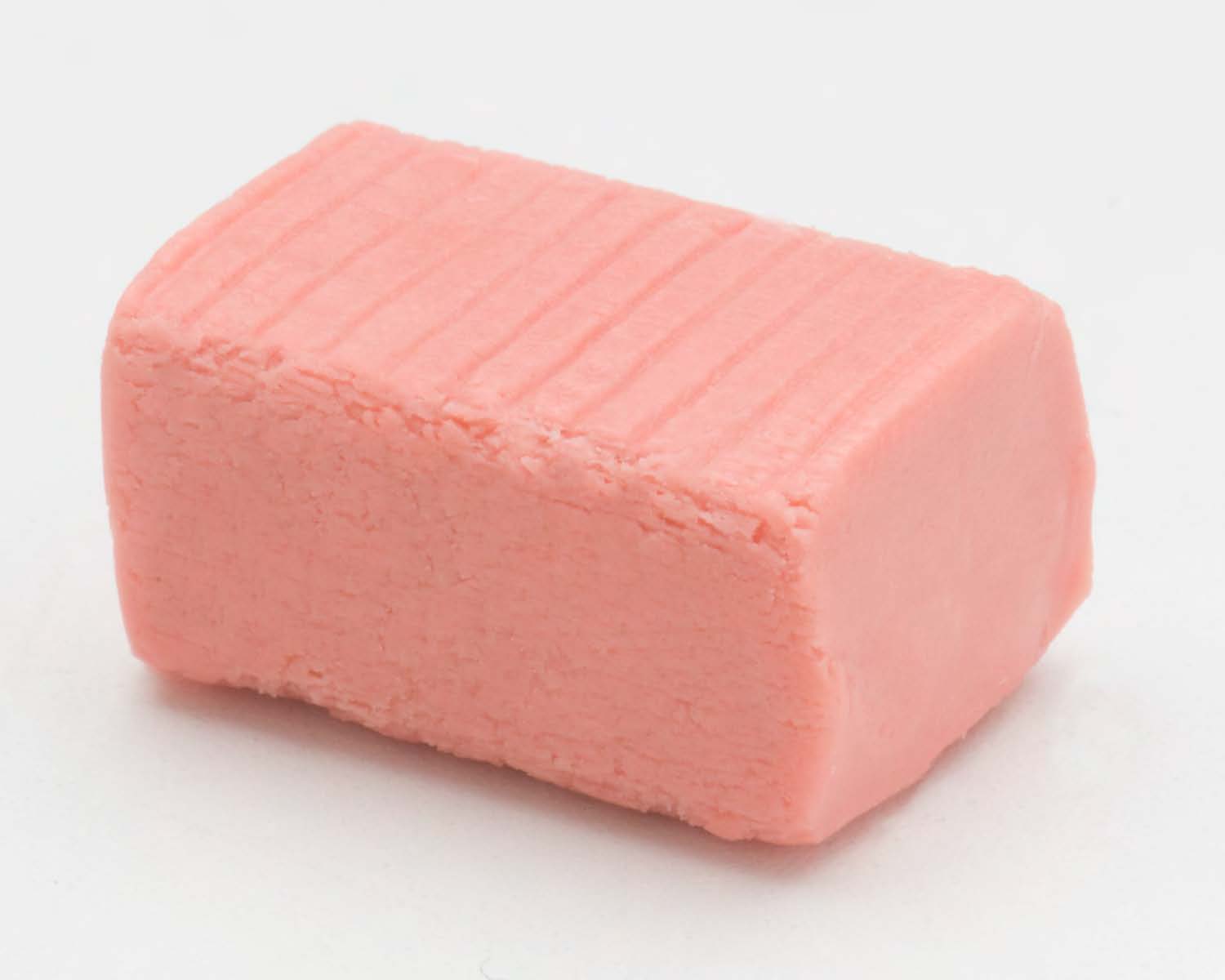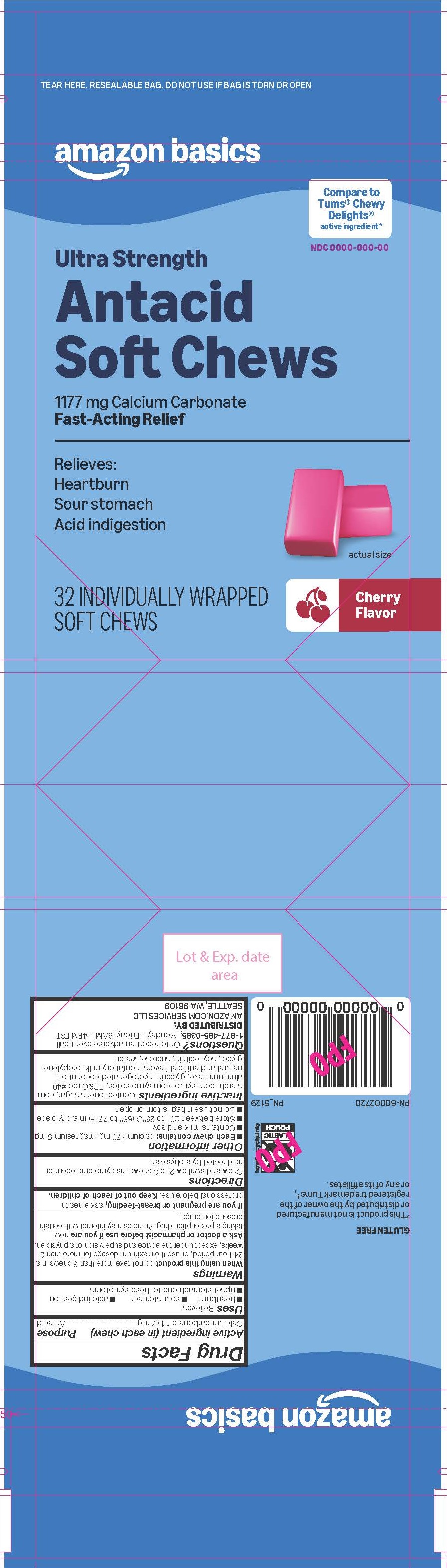 DRUG LABEL: Amazon Basics Cherry Antacid SC
NDC: 72288-240 | Form: TABLET, CHEWABLE
Manufacturer: Amazon
Category: otc | Type: HUMAN OTC DRUG LABEL
Date: 20260218

ACTIVE INGREDIENTS: CALCIUM CARBONATE 1177 mg/1 1
INACTIVE INGREDIENTS: SUCROSE

Calcium Carbonate 1177 mg

Active ingredient (in each chew)

Calcium carbonate 1177 mg

Purpose

Antacid

INDICATIONS AND USAGE

Uses Relieves

- heartburn
- sour stomach
- acid indigestion
- upset stomach due to these symptoms

Warnings

Ask a doctor or pharmacist before use if you are now taking a prescription drug. Antacids may intereact with certain prescription drugs.

When using this product do not take more than 6 chews in a 24-hour period, or use the maximum dosage for more than 2 weeks, except under the advice and supervision of a physician.

PREGNANCY OR BREAST FEEDING

If you are pregnant or breast-feeding, ask a health professional before use.

Keep out of reach of children.

Directions

Chew and swallow 2 to 3 chews, as symptoms occur or as directed by a physician.

Other information

- Each chew contains: calcium 470 mg, magnesium 5 mg
- Contains milk and soy
- Store between 20° to 25°C (68° to 77°F) in a dry place
- Do not use if bag is torn or open

INACTIVE INGREDIENT

Inactive ingredients: Confectioner's sugar, corn starch, corn syrup, corn syrup solids, FD&C red #40 aluminum lake, glycerin, hydrogenated coconut oil, natural and artificial flavors, nonfat dry milk, propylene glycol, soy lecithin, sucrose, water.

QUESTIONS

Questions? Or to report an adverse event call 1-877-485-0385, Monday - Friday, 9AM - 4PM EST